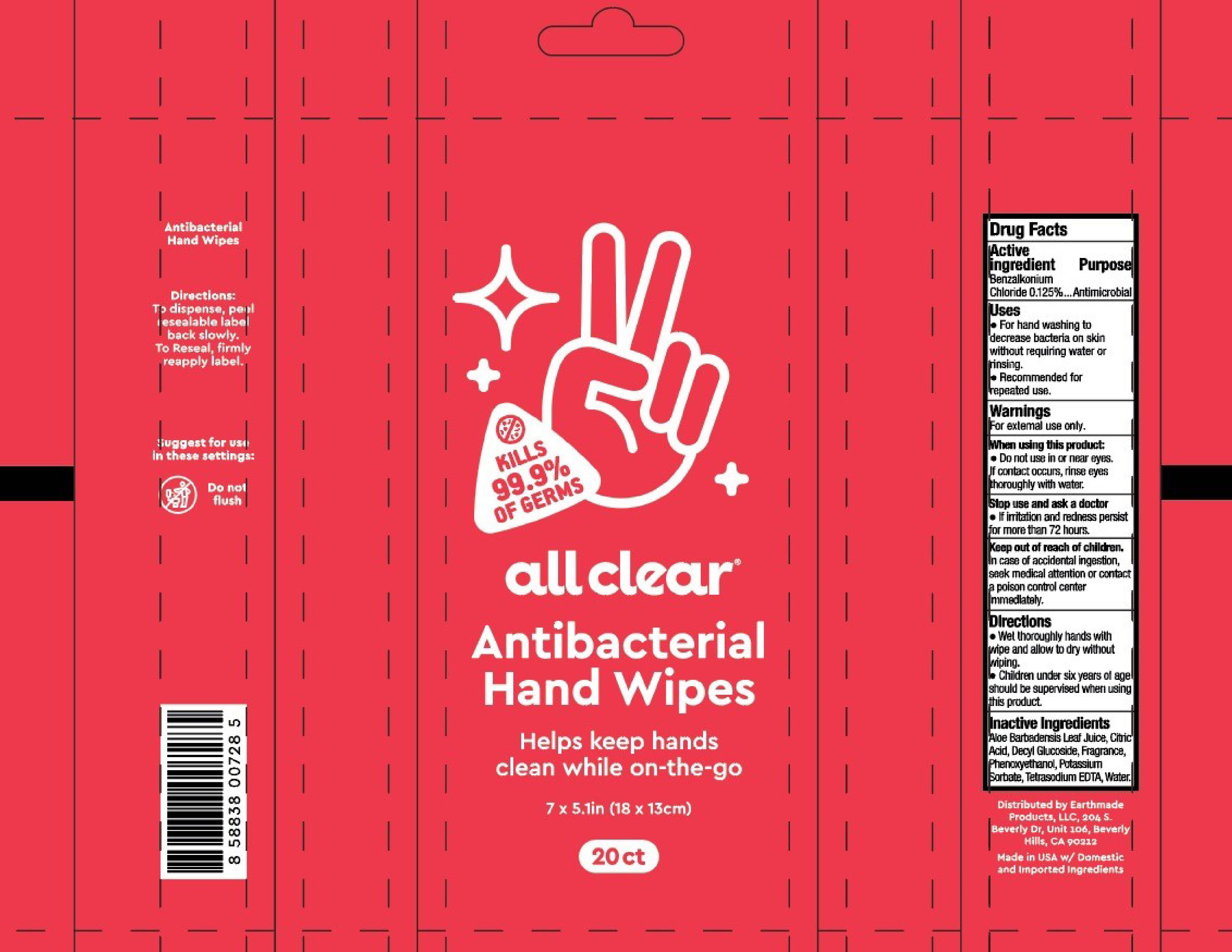 DRUG LABEL: Antimicrobial Hand Wipes
NDC: 77070-701 | Form: CLOTH
Manufacturer: Goodfibers
Category: otc | Type: HUMAN OTC DRUG LABEL
Date: 20220122

ACTIVE INGREDIENTS: BENZALKONIUM CHLORIDE 0.125 g/100 g
INACTIVE INGREDIENTS: ALOE VERA LEAF; PHENOXYETHANOL; EDETATE SODIUM; WATER; DECYL GLUCOSIDE; POTASSIUM SORBATE; ANHYDROUS CITRIC ACID

Antimicrobial Hand Wipes

Active Ingredient

Benzalkonium Chloride 0.125%

Purpose

Pupose

Antimicrobial

Uses

* For hand washing to decrease bacteria on skin without requiring water or rinsing

* Recommended for repeated use

Warnings

For external use only

When using this product

* Do not use in or near eyes

If contact occurs, rinse eyes thoroughly with water

Stop use and ask a doctor

*If irritation and redness persist for more than 72 hours

Keep Out of reach of children

In case of accidental ingestion, seek medical attention or contact a poison control center immediately.

Directions

* Wet thoroughly hands with wipe and allow to dry without wiping.

* Children under six years of age should be supervised when using this product

Inactive Ingredients

Aloe Barbadensis Leaf Juice, Citric Acid, Decyl Glucoside, Fragrance, Phenoxyethanol, Potassium Sorbate, Tetrasodium EDTA, Water.

Principal Display Panel

KILLS 99.9% OF GERMS

all clear

Antibacterial Hand Wipes

Helps keep hands clean while on-the-go

7 x 5.1in (18 x 13cm)

20ct